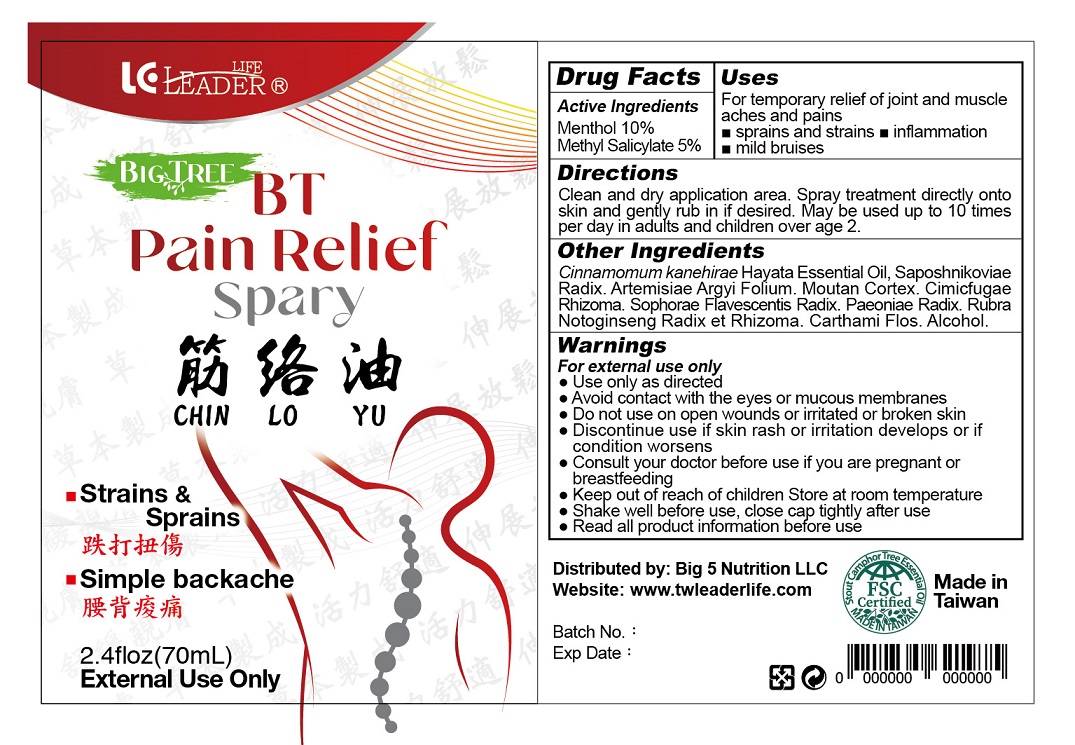 DRUG LABEL: BT Pain Relief
NDC: 82198-0012 | Form: SPRAY
Manufacturer: Big 5 Nutrition LLC
Category: otc | Type: HUMAN OTC DRUG LABEL
Date: 20231121

ACTIVE INGREDIENTS: MENTHOL, UNSPECIFIED FORM 100 mg/1 mL; METHYL SALICYLATE 50 mg/1 mL
INACTIVE INGREDIENTS: SOPHORA FLAVESCENS ROOT; PAEONIA LACTIFLORA ROOT; PANAX NOTOGINSENG ROOT; SAFFLOWER; ALCOHOL; SAPOSHNIKOVIA DIVARICATA ROOT; ARTEMISIA ARGYI LEAF; PAEONIA X SUFFRUTICOSA ROOT BARK; ACTAEA CIMICIFUGA ROOT

BT Pain Relief Spray

Active Ingredients

Menthol 10%

Methyl Salicylate 5%

Purpose

External analgesic

Uses

For temporary relief of joint and muscles aches and pains

- sprains and strains
- inflammation
- mild bruises

Warnings

For external use only

- Use only as directed
- Avoid contact with the eyes or mucous membranes
- Do not use on open wounds or irritated or broken skin.
- Discontinue use if skin rash or irritation develops or if condition worsens.
- Consult your doctor before use if you are pregnant or breast feeding.

Keep out of reach of children.

Directions

Clean and dry application area. Spray treatment directly onto skin and gently rub in if desired. May be used up to 10 times per day in adults and children over age 2.

Other Information

- Store at room temperature
- Shake well before use, close cap tightly after use
- Read all product information before use

Inactive Ingredients

Cinnamomum kanehirae Hayata Essential Oil, Saposhnikoviae Radix, Artemisia Argyi Folium, Moutan Cortex, Cimicifugae Rhizoma, Sophorae Flavescentis Radix, Paeoniae Radix, Rubra Notoginseng Radix et Rhizoma, Carthami Flos, Alcohol.

Questions or Comments?

www.twleaderlife.com

Distributed by

Big 5 Nutrition LLC

Made in Taiwan